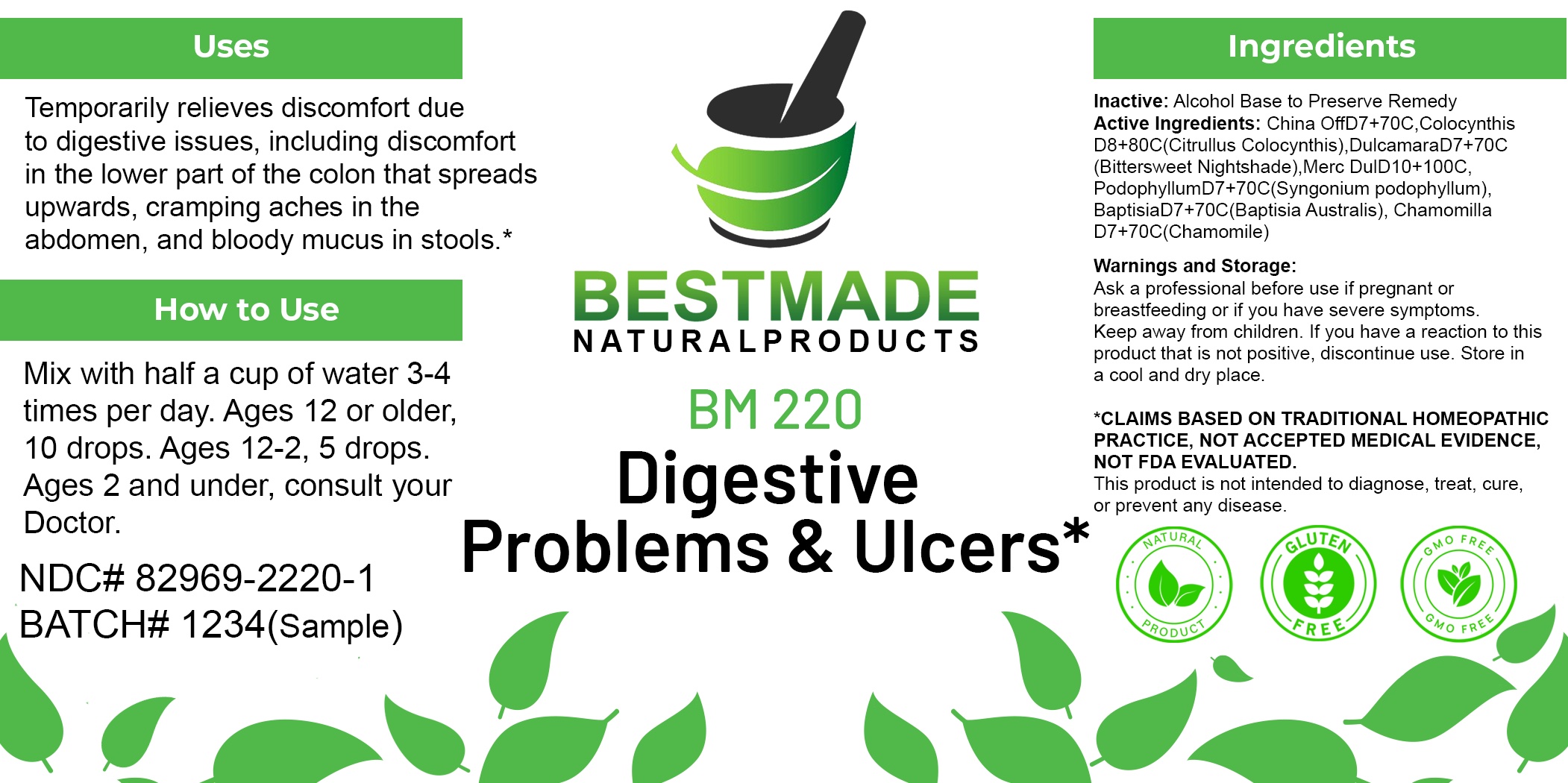 DRUG LABEL: Bestmade Natural Products BM220
NDC: 82969-2220 | Form: LIQUID
Manufacturer: Bestmade Natural Products
Category: homeopathic | Type: HUMAN OTC DRUG LABEL
Date: 20250303

ACTIVE INGREDIENTS: PODOPHYLLUM 30 [hp_C]/30 [hp_C]; CHAMOMILE 30 [hp_C]/30 [hp_C]; SOLANUM DULCAMARA FLOWER 30 [hp_C]/30 [hp_C]; BAPTISIA AUSTRALIS ROOT 30 [hp_C]/30 [hp_C]; CINCHONA OFFICINALIS BARK 30 [hp_C]/30 [hp_C]; CALOMEL 30 [hp_C]/30 [hp_C]; CITRULLUS COLOCYNTHIS FRUIT PULP 30 [hp_C]/30 [hp_C]
INACTIVE INGREDIENTS: ALCOHOL 30 [hp_C]/30 [hp_C]

BM220

DOSAGE AND ADMINISTRATION

How to Use

Mix with half a cup of water 3-4 times per day. Ages 12 or older, 10 drops. Ages 12-2, 5 drops. Ages 2 and under, consult your Doctor.

Inactive:

Alcohol Base to Preserve Product

ACTIVE INGREDIENTS

China OffD7 70C, ColocynthisD8 80C, DulcamaraD7 70C, Merc DulD10 100C, PodophyllumD7 70C, BaptisiaD7 70C, ChamomillaD7 70C

KEEP OUT OF REACH OF CHILDREN

Warnings and Storage:

Ask a professional before use if pregnant or breastfeeding or if you have severe symptoms.

Keep away from children. If you have a reaction to this product that is not positive, discontinue use. Store in a cool and dry place

*CLAIMS BASED ON TRADITIONAL HOMEOPATHIC PRACTICE, NOT ACCEPTED MEDICAL EVIDENCE NOT FDA EVALUATED.
This product is not intended to diagnose, treat, cure, or prevent any disease.

Warnings and Storage:

Ask a professional before use if pregnant or breastfeeding or if you have severe symptoms.

Keep away from children. If you have a reaction to this product that is not positive, discontinue use. Store in a cool and dry place

*CLAIMS BASED ON TRADITIONAL HOMEOPATHIC PRACTICE, NOT ACCEPTED MEDICAL EVIDENCE NOT FDA EVALUATED.
This product is not intended to diagnose, treat, cure, or prevent any disease.

Use:

Temporarily relieves discomfort due to digestive issues, including discomfort in the lower part of the colon that spreads upwards, cramping aches in the abdomen, and bloody mucus in stools.*

INDICATIONS AND USAGE

Use: Temporarily relieves discomfort due to digestive issues, including discomfort in the lower part of the colon that spreads upwards, cramping aches in the abdomen, and bloody mucus in stools.*

Entire package label